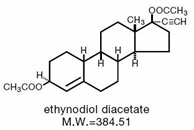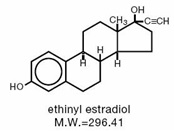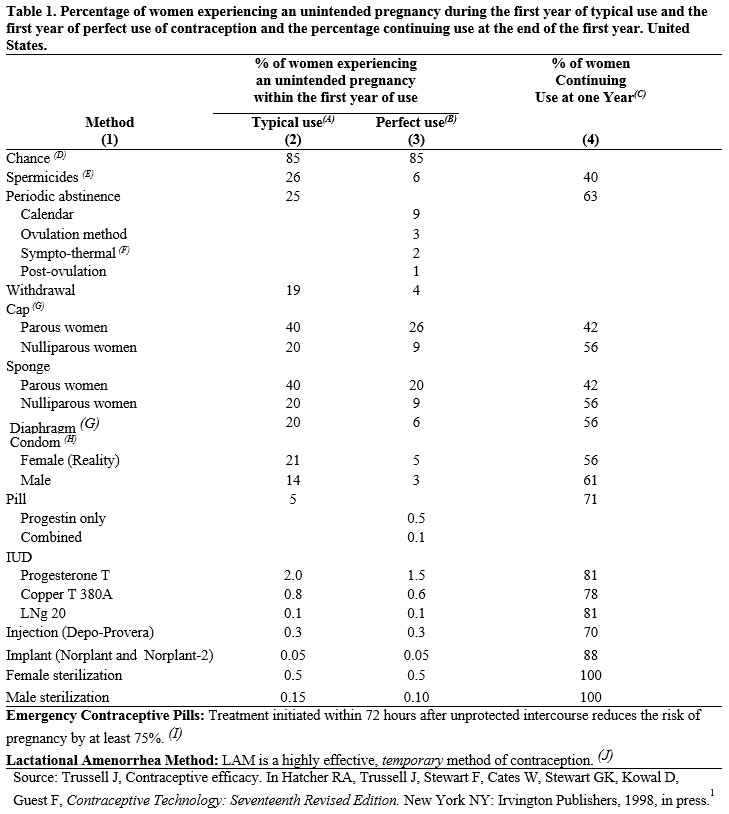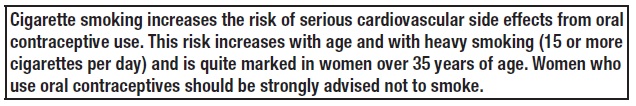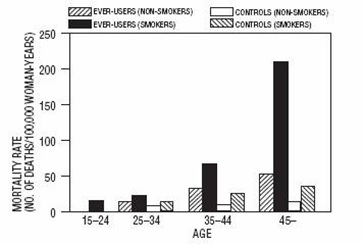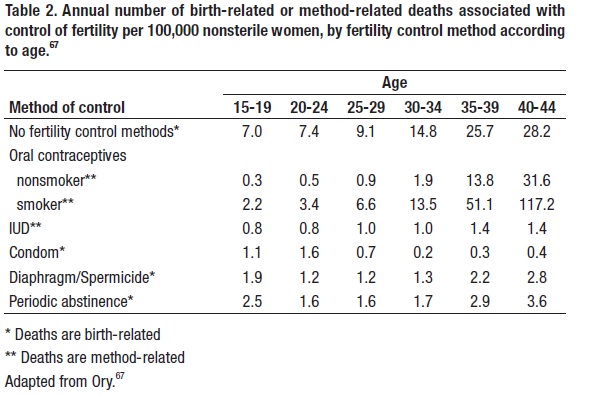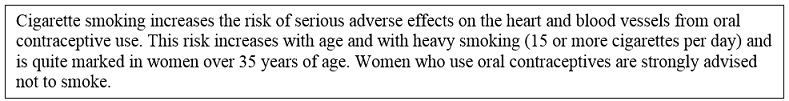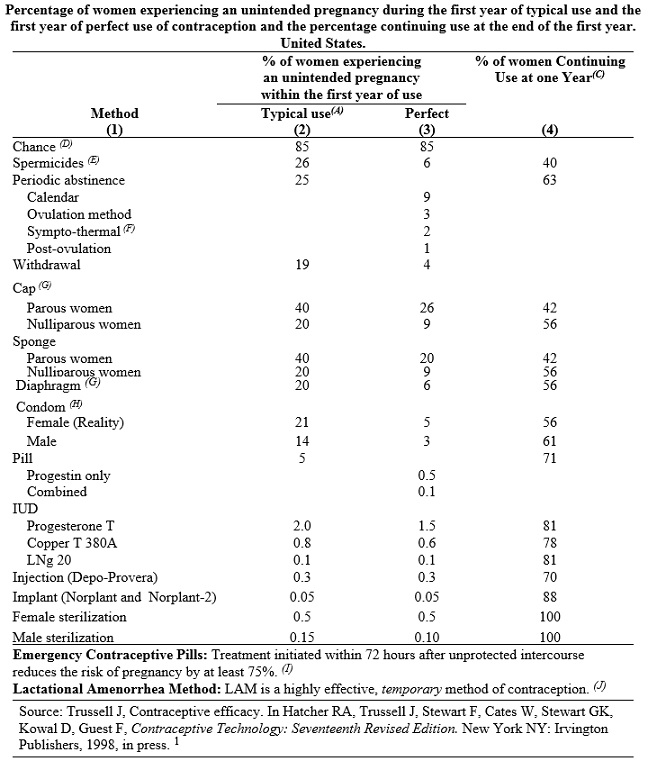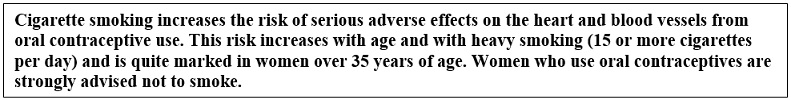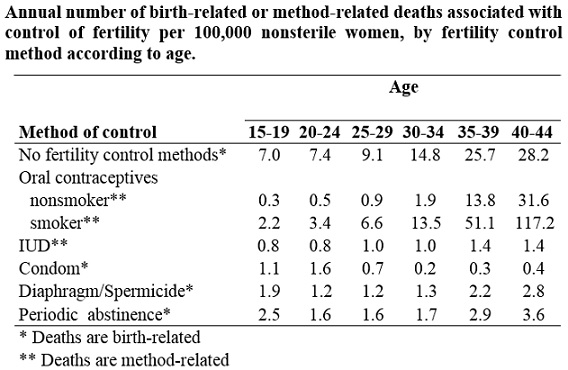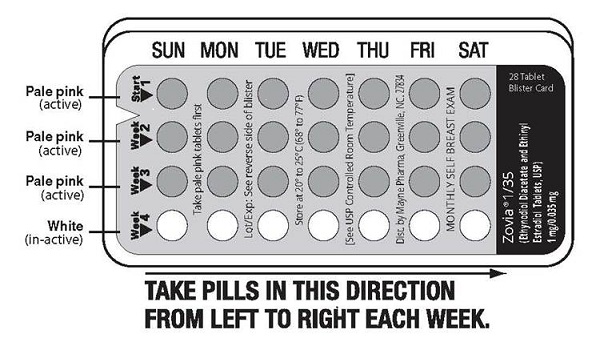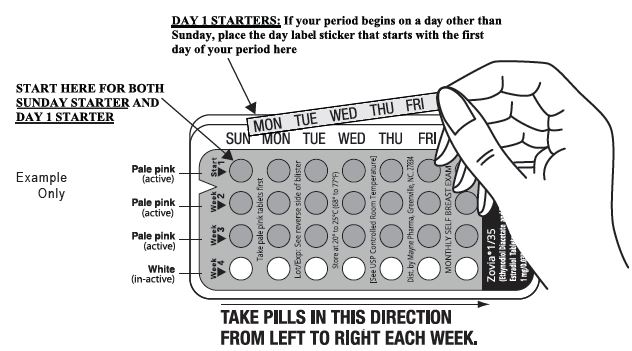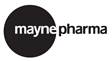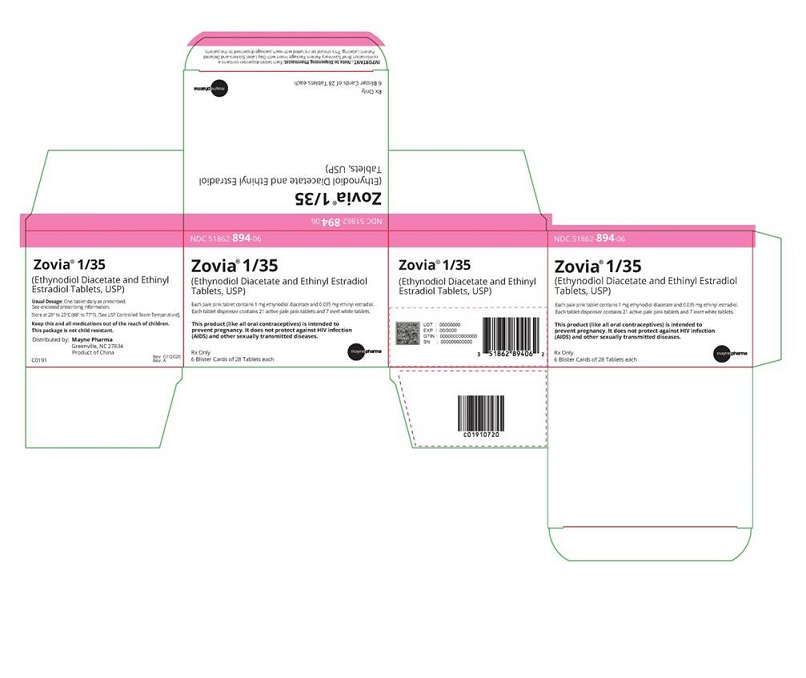 DRUG LABEL: Zovia 1/35
								
NDC: 51862-894 | Form: KIT | Route: ORAL
Manufacturer: Mayne Pharma Inc.
Category: prescription | Type: HUMAN PRESCRIPTION DRUG LABEL
Date: 20251110

ACTIVE INGREDIENTS: ETHYNODIOL DIACETATE 1 mg/1 1; ETHINYL ESTRADIOL 0.035 mg/1 1
INACTIVE INGREDIENTS: LACTOSE MONOHYDRATE; STARCH, PREGELATINIZED CORN; ALPHA-TOCOPHEROL; MAGNESIUM STEARATE; CELLULOSE, MICROCRYSTALLINE; CROSCARMELLOSE SODIUM; POVIDONE; POLYVINYL ALCOHOL; TITANIUM DIOXIDE; TALC; POLYETHYLENE GLYCOL 3350; LECITHIN, SOYBEAN; FD&C RED NO. 40; FD&C BLUE NO. 1; FD&C YELLOW NO. 6; LACTOSE MONOHYDRATE; MAGNESIUM STEARATE; STARCH, PREGELATINIZED CORN; TITANIUM DIOXIDE; POLYDEXTROSE; HYPROMELLOSES; TRIACETIN; POLYETHYLENE GLYCOL 8000

Zovia® 1/35
(Ethynodiol Diacetate and Ethinyl Estradiol Tablets USP, 1 mg/35 mcg)
Rx only

Patients should be counseled that this product does not protect against HIV infection (AIDS) and other sexually transmitted diseases.

DESCRIPTION

Zovia 1/35: Each pale pink tablet contains 1 mg of ethynodiol diacetate and 35 mcg of ethinyl estradiol, and the inactive ingredients include lactose monohydrate, pregelatinized starch, vitamin e, magnesium stearate, microcrystalline cellulose, croscarmellose sodium, povidone, polyvinyl alcohol, titanium dioxide, talc, polyethylene glycol/macrogol, lecithin (soya), FD&C Red #40 aluminum lake, FD&C Blue #1 aluminum lake, and FD&C yellow #6 aluminum lake. Each white tablet in the Zovia 1/35 package is a placebo containing no active ingredients and the inactive ingredients include lactose monohydrate, magnesium stearate, pregelatinized starch, titanium dioxide, polydextrose, hypromellose, triacetin, and polyethylene glycol.

The chemical name for ethynodiol diacetate is 19-Nor-17α-pregn-4-en-20-yne-3β,17-diol diacetate, and for ethinyl estradiol it is 19-Nor-17α-pregna-1,3,5(10)-trien-20-yne-3,17-diol.

The structural formulas are as follows:

Therapeutic class: Oral contraceptive.

CLINICAL PHARMACOLOGY

Combination oral contraceptives act primarily by suppression of gonadotropins. Although the primary mechanism of this action is inhibition of ovulation, other alterations in the genital tract, including changes in the cervical mucus (which increase the difficulty of sperm entry into the uterus) and the endometrium (which may reduce the likelihood of implantation) may also contribute to contraceptive effectiveness.

INDICATIONS AND USAGE

Zovia 1/35 is indicated for the prevention of pregnancy in women who elect to use oral contraceptives as a method of contraception.

Oral contraceptives are highly effective. Table 1 lists the typical accidental pregnancy rates for users of combination oral contraceptives and other methods of contraception. The efficacy of these contraceptive methods, except sterilization and progestogen implants and injections, depends upon the reliability with which they are used. Correct and consistent use of methods can result in lower failure rates.

(A) Among typical couples who initiate use of a method (not necessarily for the first time), the percentage who experience an accidental pregnancy during the first year if they do not stop use for any other reason.

(B) Among couples who initiate use of a method (not necessarily for the first time) and who use it perfectly (both consistently and correctly), the percentage who experience an accidental pregnancy during the first year if they do not stop use for any other reason.

(C) Among couples attempting to avoid pregnancy, the percentage who continue to use a method for one year.

(D) The percents becoming pregnant in columns (2) and (3) are based on data from populations where contraception is not used and from women who cease using contraception in order to become pregnant. Among such populations, about 89% become pregnant within one year. This estimate was lowered slightly (to 85%) to represent the percent who would become pregnant within one year among women now relying on reversible methods of contraception if they abandoned contraception altogether.

(E) Foams, creams, gels, vaginal suppositories, and vaginal film.

(F) Cervical mucus (ovulation) method supplemented by calendar in the pre-ovulatory and basal body temperature in the post-ovulatory phases.

(G) With spermicidal cream or jelly.

(H) Without spermicides.

(I) The treatment schedule is one dose within 72 hours after unprotected intercourse and a second dose 12 hours after the first dose. The Food and Drug Administration has declared the following brands of oral contraceptives to be safe and effective for emergency contraception: Ovral (1 dose is 2 white pills), Alesse (1 dose is 5 pink pills), Nordette or Levlen (1 dose is 2 light-orange pills), Lo/Ovral (1 dose is 4 white pills), Triphasil or Tri-Levlen (1 dose is 4 yellow pills).

(J) However, to maintain effective protection against pregnancy, another method of contraception must be used as soon as menstruation resumes, the frequency or duration of breastfeeds is reduced, bottle feeds are introduced, or the baby reaches six months of age.

CONTRAINDICATIONS

Oral contraceptives should not be used in women who have the following conditions:

● Thrombophlebitis or thromboembolic disorders

● A past history of deep vein thrombophlebitis or thromboembolic disorders

● Cerebral vascular disease, myocardial infarction, or coronary artery disease, or a past history of these conditions

● Known or suspected carcinoma of the breast, or a history of this condition

● Known or suspected carcinoma of the female reproductive organs or suspected estrogen-dependent neoplasia, or a history of these conditions

● Undiagnosed abnormal genital bleeding

● History of cholestatic jaundice of pregnancy or jaundice with prior oral contraceptive use

● Past or present, benign or malignant liver tumors

● Known or suspected pregnancy

● Are receiving Hepatitis C drug combinations containing ombitasvir/paritaprevir/ritonavir, with or without dasabuvir, due to the potential for ALT elevations (see Warnings, RISK OF LIVER ENZYME ELEVATIONS WITH CONCOMITANT HEPATITIS C TREATMENT)

WARNINGS

The use of oral contraceptives is associated with increased risk of several serious conditions including venous and arterial thromboembolism, thrombotic and hemorrhagic stroke, myocardial infarction, liver tumors or other liver lesions, and gallbladder disease. The risk of morbidity and mortality increases significantly in the presence of other risk factors such as hypertension, hyperlipidemia, obesity, and diabetes mellitus.

Practitioners prescribing oral contraceptives should be familiar with the following information relating to these and other risks.

The information contained herein is principally based on studies carried out in patients who used oral contraceptives with formulations containing higher amounts of estrogens and progestogens than those in common use today. The effect of long-term use of the oral contraceptives with lesser amounts of both estrogens and progestogens remains to be determined.

Throughout this labeling, epidemiological studies reported are of two types: retrospective casecontrol studies and prospective cohort studies. Case-control studies provide an estimate of the relative risk of a disease, which is defined as the ratio of the incidence of a disease among oral contraceptive users to that among nonusers. The relative risk (or odds ratio) does not provide information about the actual clinical occurrence of a disease. Cohort studies provide a measure of both the relative risk and the attributable risk. The latter is the difference in the incidence of disease between oral contraceptive users and nonusers. The attributable risk does provide information about the actual occurrence or incidence of a disease in the subject population. For further information, the reader is referred to a text on epidemiological methods.

1. Thromboembolic disorders and other vascular problems.

a. Myocardial infarction.

An increased risk of myocardial infarction has been associated with oral contraceptive use.^2-21 This increased risk is primarily in smokers or in women with other underlying risk factors for coronary artery disease such as hypertension, obesity, diabetes, and hypercholesterolemia. The relative risk for myocardial infarction in current oral contraceptive users has been estimated to be 2 to 6. The risk is very low under the age of 30. However, there is the possibility of a risk of cardiovascular disease even in very young women who take oral contraceptives.

Smoking in combination with oral contraceptive use has been reported to contribute substantially to the risk of myocardial infarction in women in their mid-thirties or older, with smoking accounting for the majority of excess cases.^22 Mortality rates associated with circulatory disease have been shown to increase substantially in smokers, especially in those 35 years of age and older among women who use oral contraceptives (see Figure 1, Table 2).

Figure 1. Circulatory disease mortality rates per 100,000 woman-years by age, smoking status, and oral contraceptive use.^14

Adapted from Layde and Beral.^14

Oral contraceptives may compound the effects of well-known cardiovascular risk factors such as hypertension, diabetes, hyperlipidemias, hypercholesterolemia, age, cigarette smoking, and obesity. In particular, some progestogens decrease HDL cholesterol^23-31 and cause glucose intolerance, while estrogens may create a state of hyperinsulinism.^32 Oral contraceptives have been shown to increase blood pressure among some users (see WARNING No. 10). Similar effects on risk factors have been associated with an increased risk of heart disease.

b. Thromboembolism.

An increased risk of thromboembolic and thrombotic disease associated with the use of oral contraceptives is well established.17, 33-51 Case-control studies have estimated the relative risk to be 3 for the first episode of superficial venous thrombosis, 4 to 11 for deep vein thrombosis or pulmonary embolism, and 1.5 to 6 for women with predisposing conditions for venous thromboembolic disease.^(34-37, 45, 46) Cohort studies have shown the relative risk to be somewhat lower, about 3 for new cases (subjects with no past history of venous thrombosis or varicose veins) and about 4.5 for new cases requiring hospitalization.^(42, 47, 48) The risk of venous thromboembolic disease associated with oral contraceptives is not related to duration of use.

A two- to seven-fold increase in relative risk of postoperative thromboembolic complications has been reported with the use of oral contraceptives.^(38, 39)The relative risk of venous thrombosis in women who have predisposing conditions is about twice that of women without such medical conditions.^43 If feasible, oral contraceptives should be discontinued at least 4 weeks prior to and for 2 weeks after elective surgery of a type associated with an increased risk of thromboembolism, and also during and following prolonged immobilization. Since the immediate postpartum period is also associated with an increased risk of thromboembolism, oral contraceptives should be started no earlier than 4 to 6 weeks after delivery in women who elect not to breast feed.

c. Cerebrovascular diseases.

Both the relative and attributable risks of cerebrovascular events (thrombotic and hemorrhagic strokes) have been reported to be increased with oral contraceptive use,^(14, 17, 18, 34, 42, 46, 52-59) although, in general, the risk was greatest among older (over 35 years), hypertensive women who also smoked. Hypertension was reported to be a risk factor for both users and nonusers, for both types of strokes, while smoking increased the risk for hemorrhagic strokes.

In one large study, ^52 the relative risk for thrombotic stroke was reported as 9.5 times greater in users than in nonusers. It ranged from 3 for normotensive users to 14 for users with severe hypertension.^54 The relative risk for hemorrhagic stroke was reported to be 1.2 for nonsmokers who used oral contraceptives, 1.9 to 2.6 for smokers who did not use oral contraceptives, 6.1 to 7.6 for smokers who used oral contraceptives, 1.8 for normotensive users, and 25.7 for users with severe hypertension. The risk is also greater in older women and among smokers.

d. Dose-related risk of vascular disease with oral contraceptives.

A positive association has been reported between the amount of estrogen and progestogen in oral contraceptives and the risk of vascular disease.^(41, 43, 53, 59-64) A decline in serum high density lipoproteins (HDL) has been reported with many progestogens.^23-31 A decline in serum high density lipoproteins has been associated with an increased incidence of ischemic heart disease.^65 Because estrogens increase HDL-cholesterol, the net effect of an oral contraceptive depends on the balance achieved between doses of estrogen and progestogen and the nature and absolute amount of progestogens used in the contraceptives. The amount of both steroids should be considered in the choice of an oral contraceptive.

Minimizing exposure to estrogen and progestogen is in keeping with good principles of therapeutics. For any particular estrogen-progestogen combination, the dosage regimen prescribed should be one that contains the least amount of estrogen and progestogen that is compatible with a low failure rate and the needs of the individual patient. New acceptors of oral contraceptives should be started on preparations containing the lowest estrogen content that produces satisfactory results in the individual.

e. Persistence of risk of vascular disease.

There are three studies that have shown persistence of risk of vascular disease for users of oral contraceptives. In a study in the United States, the risk of developing myocardial infarction after discontinuing oral contraceptives persisted for at least 9 years for women 40-49 years old who had used oral contraceptives for 5 or more years, but this increased risk was not demonstrated in other age groups.^16 Another American study reported former use of oral contraceptives was significantly associated with increased risk of subarachnoid hemorrhage.^57 In another study, in Great Britain, the risk of developing non-rheumatic heart disease plus hypertension, subarachnoid hemorrhage, cerebral thrombosis, and transient ischemic attacks persisted for at least 6 years after discontinuation of oral contraceptives, although the excess risk was small.^(14, 18, 66) It should be noted that these studies were performed with oral contraceptive formulations containing 50 mcg or more of estrogens.

2. Estimates of mortality from contraceptive use.

One study^67 gathered data from a variety of sources that have estimated the mortality rates associated with different methods of contraception at different ages (Table 2). These estimates include the combined risk of death associated with contraceptive methods plus the risk attributable to pregnancy in the event of method failure. Each method of contraception has its specific benefits and risks. The study concluded that, with the exception of oral contraceptive users 35 and older who smoke and 40 or older who do not smoke, mortality associated with all methods of birth control is low and below that associated with childbirth. The observation of a possible increase in risk of mortality with age for oral contraceptive users is based on data gathered in the 1970's, but not reported until 1983.^67 However, current clinical practice involves the use of lower estrogen dose formulations combined with careful restriction of oral contraceptive use to women who do not have the various risk factors listed in this labeling.

Because of these changes in practice and, also, because of some limited new data that suggest that the risk of cardiovascular disease with the use of oral contraceptives may now be less than previously observed,^48,152 the Fertility and Maternal Health Drugs Advisory Committee was asked to review the topic in 1989. The Committee concluded that, although cardiovascular disease risks may be increased with oral contraceptive use after age 40 in healthy nonsmoking women (even with the newer low-dose formulations), there are greater potential health risks associated with pregnancy in older women and with the alternative surgical and medical procedures that may be necessary if such women do not have access to effective and acceptable means of contraception.

Therefore, the Committee recommended that the benefits of oral contraceptive use by healthy nonsmoking women over 40 may outweigh the possible risks. Of course, older women, as all women who take oral contraceptives, should take the lowest possible dose formulation that is effective.

3. Carcinoma of the breast and reproductive organs.

Numerous epidemiological studies have been performed on the incidence of breast, endometrial, ovarian, and cervical cancer in women using oral contraceptives. While there are conflicting reports, many studies suggest that the use of oral contraceptives is not associated with an overall increase in the risk of developing breast cancer.^(17, 40, 68-78) Other studies, however, have reported an increased risk overall,^153-155 or in certain subgroups. In these studies, increased risk has been associated with long duration of use, use beginning at a young age, use before the first term pregnancy, use by those who had an early menarche, those who had a positive family history of breast cancer, or in nulliparas.^(79-102, 151, 156-162) These risks have been surveyed in two books^163-164 and in review articles.^(85, 99, 153, 165-167)

Some studies suggested that oral contraceptive use was associated with an increase in the risk of cervical intraepithelial neoplasia, dysplasia, erosion, carcinoma, or microglandular dysplasia in some populations of women.^(17, 50, 103-115) However, there continues to be controversy about the extent to which such findings may be due to differences in sexual behavior and other factors.

In spite of many studies of the relationship between oral contraceptive use and breast and cervical cancers, a cause and effect relationship has not been established.

4. Hepatic neoplasia.

Benign hepatic adenomas and other hepatic lesions have been associated with oral contraceptive use, ^116-121 although the incidence of such benign tumors is rare in the United States. Indirect calculations have estimated the attributable risk to be in the range of 3.3 cases per 100,000 for users, a risk that increases after 4 or more years of use.^120 Rupture of benign, hepatic adenomas or other lesions may cause death through intraabdominal hemorrhage. Therefore, such lesions should be considered in women presenting with abdominal pain and tenderness, abdominal mass, or shock. About one quarter of the cases presented because of abdominal masses; up to one half had signs and symptoms of acute intraperitoneal hemorrhage.^121 Diagnosis may prove difficult.

Studies from the U.S.,^(122, 150) Great Britain,^(123, 124) and Italy^125 have shown an increased risk of hepatocellular carcinoma in long-term (>8 years; relative risk of 7-20) oral contraceptive users. However, these cancers are rare in the United States, and the attributable risk (the excess incidence) of liver cancers in oral contraceptive users approaches less than 1 per 1,000,000 users.

5. Risk of liver enzyme elevations with concomitant hepatitis C treatment

During clinical trials with the Hepatitis C combination drug regimen that contains ombitasvir/paritaprevir/ ritonavir, with or without dasabuvir, ALT elevations greater than 5 times the upper limit of normal (ULN) including some cases greater than 20 times the ULN, were significantly more frequent in women using ethinyl estradiol-containing medications suchs as COCs. Discontinue Zovia 1/35 prior to starting therapy with the combination drug regimen ombitasvir/paritaprevir/ritonavir, with or without dasabuvir [see Contraindications]. Zovia 1/35 can be restarted approximately 2 weeks following completion of treatment with the combination drug regimen.

6. Ocular lesions.

There have been reports of retinal thrombosis and other ocular lesions associated with the use of oral contraceptives. Oral contraceptives should be discontinued if there is unexplained, gradual or sudden, partial or complete loss of vision; onset of proptosis or diplopia; papilledema; or any evidence of retinal vascular lesions. Appropriate diagnostic and therapeutic measures should be undertaken immediately.

7. Oral contraceptive use before or during pregnancy.

Extensive epidemiological studies have revealed no increased risk of birth defects in women who have used oral contraceptives prior to pregnancy.^(126, 129) The majority of recent studies also do not suggest a teratogenic effect, particularly insofar as cardiac anomalies and limb reduction defects are concerned, ^(126, 129) when the pill is taken inadvertently during early pregnancy.

The administration of oral contraceptives to induce withdrawal bleeding should not be used as a test for pregnancy. Oral contraceptives should not be used during pregnancy to treat threatened or habitual abortion. It is recommended that for any patient who has missed two consecutive periods, pregnancy should be ruled out before continuing oral contraceptive use. If the patient has not adhered to the prescribed schedule, the possibility of pregnancy should be considered at the time of the first missed period and further use of oral contraceptives should be withheld until pregnancy has been ruled out. Oral contraceptive use should be discontinued if pregnancy is confirmed.

8. Gallbladder disease.

Earlier studies reported an increased lifetime relative risk of gallbladder surgery in users of oral contraceptives and estrogens.^(40, 42, 53, 70) More recent studies, however, have shown that the relative risk of developing gallbladder disease among oral contraceptive users may be minimal.^130-132 The recent findings of minimal risk may be related to the use of oral contraceptive formulations containing lower doses of estrogens and progestogens.

9. Carbohydrate and lipid metabolic effects.

Oral contraceptives have been shown to cause a decrease in glucose tolerance in a significant percentage of users.^32 This effect has been shown to be directly related to estrogen dose.^133 Progestogens increase insulin secretion and create insulin resistance, the effect varying with different progestational agents.^(32, 134) However, in the nondiabetic woman, oral contraceptives appear to have no effect on fasting blood glucose. Because of these demonstrated effects, prediabetic and diabetic women should be carefully observed while taking oral contraceptives.

Some women may have persistent hypertriglyceridemia while on the pill. As discussed earlier (see WARNINGS 1a and 1d), changes in serum triglycerides and lipoprotein levels have been reported in oral contraceptive users.^(23-31, 135, 136)

10. Elevated blood pressure.

An increase in blood pressure has been reported in women taking oral contraceptives^(50, 53, 137-139) and this increase is more likely in older oral contraceptive users^137 and with extended duration of use.^53 Data from the Royal College of General Practitioners^138 and subsequent randomized trials have shown that the incidence of hypertension increases with increasing concentrations of progestogens.

Women with a history of hypertension or hypertension-related disease, or renal disease^139 should be encouraged to use another method of contraception. If such women elect to use oral contraceptives, they should be monitored closely and if significant elevation of blood pressure occurs, oral contraceptives should be discontinued. For most women, elevated blood pressure will return to normal after stopping oral contraceptives,^137 and there is no difference in the occurrence of hypertension among ever- and never-users.^140

11. Headache.

The onset or exacerbation of migraine or the development of headache of a new pattern that is recurrent, persistent, or severe requires discontinuation of oral contraceptives and evaluation of the cause.

12. Bleeding irregularities.

Breakthrough bleeding and spotting are sometimes encountered in patients on oral contraceptives, especially during the first three months of use. Nonhormonal causes should be considered and adequate diagnostic measures taken to rule out malignancy or pregnancy in the event of breakthrough bleeding, as in the case of any abnormal vaginal bleeding. If a pathologic basis has been excluded, time alone or a change to another formulation may solve the problem. In the event of amenorrhea, pregnancy should be ruled out. Some women may encounter post-pill amenorrhea or oligomenorrhea, especially when such a condition was pre-existent.

PRECAUTIONS

1. Physical examination and follow-up.

It is good medical practice for all women to have annual history and physical examinations, including women using oral contraceptives. The physical examination, however, may be deferred until after initiation of oral contraceptives if requested by the woman and judged appropriate by the clinician. The physical examination should include special reference to blood pressure, breasts, abdomen, and pelvic organs, including cervical cytology, and relevant laboratory tests. In case of undiagnosed, persistent, or recurrent abnormal vaginal bleeding, appropriate measures should be conducted to rule out malignancy. Women with a strong family history of breast cancer or who have breast nodules should be monitored with particular care.

2. Lipid disorders.

Women who are being treated for hyperlipidemias should be followed closely if they elect to use oral contraceptives. Some progestogens may elevate LDL levels and may render the control of hyperlipidemias more difficult.

3. Liver function.

If jaundice develops in any woman receiving oral contraceptives, they should be discontinued. Steroids may be poorly metabolized in patients with impaired liver function and should be administered with caution in such patients. Cholestatic jaundice has been reported after combined treatment with oral contraceptives and troleandomycin. Hepatotoxicity following a combination of oral contraceptives and cyclosporine has also been reported.

4. Fluid retention.

Oral contraceptives may cause some degree of fluid retention. They should be prescribed with caution, and only with careful monitoring, in patients with conditions that might be aggravated by fluid retention, such as convulsive disorders, migraine syndrome, asthma, or cardiac, hepatic, or renal dysfunction.

5. Emotional disorders.

Women with a history of depression should be carefully observed and the drug discontinued if depression recurs to a serious degree.

6. Contact lenses.

Contact lens wearers who develop visual changes or changes in lens tolerance should be assessed by an ophthalmologist.

7. Drug interactions.

Reduced efficacy and increased incidence of breakthrough bleeding and menstrual irregularities have been associated with concomitant use of rifampin. A similar association, though less marked, has been suggested for barbiturates, phenylbutazone, phenytoin sodium, and possibly with griseofulvin, ampicillin, and tetracyclines. Administration of troglitazone concomitantly with a combination oral contraceptive (estrogen and progestin) reduced the plasma concentrations of both hormones by approximately 30%. This could result in loss of contraceptive efficacy.

Concomitant Use with HCV Combination Therapy – Liver Enzyme Elevation

Do not co-administer Zovia 1/35 with HCV drug combinations containing ombitasvir/paritaprevir/ritonavir, with or without dasabuvir, due to potential for ALT elevations (see Warnings, RISK OF LIVER ENZYME ELEVATIONS WITH CONCOMITANT HEPATITIS C TREATMENT).

8. Laboratory test interactions.

Certain endocrine and liver function tests and blood components may be affected by oral contraceptives:

a. Increased prothrombin and factors VII, VIII, IX and X; decreased antithrombin III; increased platelet aggregability.

b. Increased thyroid binding globulin (TBG), leading to increased circulating total thyroid hormone as measured by protein-bound iodine (PBI), T4 by column or by radioimmunoassay. Free T3 resin uptake is decreased, reflecting the elevated TBG; free T4 concentration is unaltered.

c. Other binding proteins may be elevated in the serum.

d. Sex-steroid binding globulins are increased and result in elevated levels of total circulating sex steroids and corticoids; however, free or biologically active levels remain unchanged.

e. Triglycerides and phospholipids may be increased.

f. Glucose tolerance may be decreased.

g. Serum folate levels may be depressed. This may be of clinical significance if a woman becomes pregnant shortly after discontinuing oral contraceptives.

h. Increased sulfobromophthalein and other abnormalities in liver function tests may occur.

i. Plasma levels of trace minerals may be altered.

j. Response to the metyrapone test may be reduced.

9. Carcinogenesis.

(See WARNINGS.)

10. Pregnancy.

Pregnancy Category X. (See CONTRAINDICATIONS and WARNINGS.)

11. Nursing mothers.

Small amounts of oral contraceptive steroids have been identified in the milk of nursing mothers^141-143 and a few adverse effects on the child have been reported, including jaundice and breast enlargement. In addition, oral contraceptives given in the postpartum period may interfere with lactation by decreasing the quantity and quality of breast milk. If possible, the nursing mother should be advised not to use oral contraceptives, but to use other forms of contraception until she has completely weaned her child.

12. Pediatric use.

Safety and efficacy of Zovia 1/35 have been established in women of reproductive age. Safety and efficacy are expected to be the same for postpubertal adolescents under the age of 16 and for users 16 years and older. Use of this product before menarche is not indicated.

13. Venereal diseases.

Oral contraceptives are of no value in the prevention or treatment of venereal disease. The prevalence of cervical Chlamydia trachomatis and Neisseria gonorrhoeae in oral contraceptive users is increased several-fold.^(144, 145) It should not be assumed that oral contraceptives afford protection against pelvic inflammatory disease from chlamydia.144 Patients should be counseled that this product does not protect against HIV infection (AIDS) and other sexually transmitted diseases.

14. General.

a. The pathologist should be advised of oral contraceptive therapy when relevant specimens are submitted.

b. Treatment with oral contraceptives may mask the onset of the climacteric. (See WARNINGS regarding risks in this age group.)

INFORMATION FOR PATIENTS

See patient labeling printed below.

ADVERSE REACTIONS

An increased risk of the following serious adverse reactions has been associated with the use of oral contraceptives (see WARNINGS):

● Thrombophlebitis and thrombosis

● Arterial thromboembolism

● Pulmonary embolism

● Myocardial infarction and coronary thrombosis

● Cerebral hemorrhage

● Cerebral thrombosis

● Hypertension

● Gallbladder disease

● Benign and malignant liver tumors, and other hepatic lesions

There is evidence of an association between the following conditions and the use of oral contraceptives, although additional confirmatory studies are needed:

● Mesenteric thrombosis

● Neuro-ocular lesions (e.g., retinal thrombosis and optic neuritis)

The following adverse reactions have been reported in patients receiving oral contraceptives and are believed to be drug-related:

● Nausea

● Vomiting

● Gastrointestinal symptoms (such as abdominal cramps and bloating)

● Breakthrough bleeding

● Spotting

● Change in menstrual flow

● Amenorrhea during or after use

● Temporary infertility after discontinuation of use

● Edema

● Chloasma or melasma, which may persist

● Breast changes: tenderness, enlargement, secretion

● Change in weight (increase or decrease)

● Change in cervical erosion or secretion

● Diminution in lactation when given immediately postpartum

● Cholestatic jaundice

● Migraine

● Rash (allergic)

● Mental depression

● Reduced tolerance to carbohydrates

● Vaginal candidiasis

● Change in corneal curvature (steepening)

● Intolerance to contact lenses

The following adverse reactions or conditions have been reported in users of oral contraceptives and the association has been neither confirmed nor refuted:

● Premenstrual syndrome

● Cataracts

● Changes in appetite

● Cystitis-like syndrome

● Headache

● Nervousness

● Dizziness

● Hirsutism

● Loss of scalp hair

● Erythema multiforme

● Erythema nodosum

● Hemorrhagic eruption

● Vaginitis

● Porphyria

● Impaired renal function

● Hemolytic uremic syndrome

● Acne

● Changes in libido

● Colitis

● Budd-Chiari syndrome

● Endocervical hyperplasia or ectropion

OVERDOSAGE

Serious ill effects have not been reported following acute ingestion of large doses of oral contraceptives by young children.^(180, 181) Overdosage may cause nausea, and withdrawal bleeding may occur in females.

NON-CONTRACEPTIVE HEALTH BENEFITS

The following non-contraceptive health benefits related to the use of oral contraceptives are supported by epidemiological studies that largely utilized oral contraceptive formulations containing estrogen doses exceeding 35 mcg of ethinyl estradiol or 50 mcg of mestranol.^(148, 149)

Effects on menses:

● Increased menstrual cycle regularity

● Decreased blood loss and decreased risk of iron-deficiency anemia

● Decreased frequency of dysmenorrhea

Effects related to inhibition of ovulation:

● Decreased risk of functional ovarian cysts

● Decreased risk of ectopic pregnancies

Effects from long-term use:

● Decreased risk of fibroadenomas and fibrocystic disease of the breast

● Decreased risk of acute pelvic inflammatory disease

● Decreased risk of endometrial cancer

● Decreased risk of ovarian cancer

● Decreased risk of uterine fibroids

DOSAGE AND ADMINISTRATION

To achieve maximum contraceptive effectiveness, oral contraceptives must be taken exactly as directed and at intervals of 24 hours.

IMPORTANT: If the Sunday start schedule is selected, the patient should be instructed to use an additional method of protection until after the first week of administration in the initial cycle.

The possibility of ovulation and conception prior to initiation of use should be considered.

Zovia 1/35

Dosage Schedules

The Zovia 1/35 tablet dispensers contain 21 pale pink active tablets arranged in three numbered rows of 7 tablets each, followed by a fourth row of 7 white placebo (inactive) tablets .

Days of the week are embossed on the plastic compact just above the tablets, starting with Sunday on the left.

28-Day Schedule: For a DAY 1 START, count the first day of menstrual flow as Day 1 and the first tablet (pale pink) is then taken on Day 1. For a SUNDAY START when menstrual flow begins on or before Sunday, the first tablet (pale pink) is taken on that day. With either a DAY 1 START or SUNDAY START, 1 tablet (pale pink) is taken each day at the same time for 21 days. Then the white tablets are taken for 7 days, whether bleeding has stopped or not. After all 28 tablets have been taken, whether bleeding has stopped or not, the same dosage schedule is repeated beginning on the following day.

Special notes

Spotting, breakthrough bleeding, or nausea. If spotting (bleeding insufficient to require a pad), breakthrough bleeding (heavier bleeding similar to a menstrual flow), or nausea occurs the patient should continue taking her tablets as directed. The incidence of spotting, breakthrough bleeding or nausea is minimal, most frequently occurring in the first cycle. Ordinarily spotting or breakthrough bleeding will stop within a week. Usually the patient will begin to cycle regularly within two or three courses of tablet-taking. In the event of spotting or breakthrough bleeding organic causes should be borne in mind. (See WARNING No. 12.)

Missed menstrual periods. Withdrawal flow will normally occur 2 or 3 days after the last active tablet is taken. Failure of withdrawal bleeding ordinarily does not mean that the patient is pregnant, providing the dosage schedule has been correctly followed. (See WARNING No. 7.)

If the patient has not adhered to the prescribed dosage regimen, the possibility of pregnancy should be considered after the first missed period, and oral contraceptives should be withheld until pregnancy has been ruled out.

If the patient has adhered to the prescribed regimen and misses two consecutive periods, pregnancy should be ruled out before continuing the contraceptive regimen.

The first intermenstrual interval after discontinuing the tablets is usually prolonged; consequently, a patient for whom a 28-day cycle is usual might not begin to menstruate for 35 days or longer. Ovulation in such prolonged cycles will occur correspondingly later in the cycle. Post-treatment cycles after the first one, however, are usually typical for the individual woman prior to taking tablets. (See WARNING No. 12.)

Missed tablets. If a woman misses taking one active tablet, the missed tablet should be taken as soon as it is remembered. In addition, the next tablet should be taken at the usual time. If two consecutive active tablets are missed in week 1 or week 2 of the dispenser, the dosage should be doubled for the next 2 days. The regular schedule should then be resumed, but an additional method of protection must be used as backup for the next 7 days if she has sex during that time or she may become pregnant.

If two consecutive active tablets are missed in week 3 of the dispenser or three consecutive active tablets are missed during any of the first 3 weeks of the dispenser, direct the patient to do one of the following: Day 1 Starters should discard the rest of the dispenser and begin a new dispenser that same day; Sunday Starters should continue to take 1 tablet daily until Sunday, discard the rest of the dispenser and begin a new dispenser that same day. The patient may not have a period this month; however, if she has missed two consecutive periods, pregnancy should be ruled out. An additional method of protection must be used as a backup for the next 7 days after the tablets are missed if she has sex during that time or she may become pregnant.

While there is little likelihood of ovulation if only one active tablet is missed, the possibility of spotting or breakthrough bleeding is increased and should be expected if two or more successive active tablets are missed. However, the possibility of ovulation increases with each successive day that scheduled active tablets are missed.

If one or more placebo tablets of Zovia 1/35 are missed, the schedule should be resumed on the eighth day after the last pale pink colored tablet was taken. Omission of placebo tablets in the 28-tablet courses does not increase the possibility of conception provided that this schedule is followed.

HOW SUPPLIED

Zovia 1/35: Each pale pink Zovia 1/35 tablet is round, biconvex, unscored, debossed with X1 on one side and contains 1 mg of ethynodiol diacetate and 35 mcg of ethinyl estradiol.

Zovia 1/35 is packaged in cartons of three (NDC 51862-894-03) and six (NDC 51862-894-06) tablet compact dispensers. Each compact dispenser contains 21 pale pink tablets and 7 white placebo tablets. Placebo tablets are round, biconvex and have a debossed P on one side and N on the other side.

Store at 20° to 25°C (68° to 77°F). [See USP controlled room temperature.]

REFERENCES

1. Hatcher RA, et al. Contraceptive Technology: Seventeenth Revised Edition. New York, NY, 1998. 1a. Physicians' Desk Reference. 47th ed. Oradell, NJ: Medical Economics Co Inc; 1993;2598-2601. 2. Mann JI, et al. Br Med J. 1975; 2 (May 3):241. 3. Mann JI, et al. Br Med J. 1975;3(Sept 13):631. 4. Mann JI, et al. Br Med J. 1975;2(May 3):245. 5. Mann JI, et al. Br Med J. 1976;2(Aug 21):445. 6. Arthes FG, et al. Chest. 1976;70(Nov):574. 7. Jain AK, Am J Obstet Gynecol. 1976;301(Oct 1):126 and Stud Fam Plann. 1977;8(March):50. 8. Ory HW. JAMA. 1977;237(June 13):2619. 9. Jick H, et al. JAMA. 1978;239(April 3):1403, 1407. 10. Jick H, et al. JAMA. 1978;240(Dec 1):2548. 11. Shapiro S, et al. Lancet. 1979;1(April 7):743. 12. Rosenberg L, et al. Am J Epidemiol. 1980;111(Jan):59. 13. Krueger DE, et al. Am J Epidemiol. 1980;111(June):655. 14. Layde P, et al. Lancet. 1981;1(March 7):541. 15. Adam SA, et al. Br J Obstet Gynaecol. 1981;88(Aug):838. 16. Slone D, et al. N Engl J Med. 1981;305 (Aug 20):420. 17. Ramcharan S, et al. The Walnut Creek Contraceptive Drug Study. Vol 3. US Govt Ptg Off. 1981; and J Reprod Med. 1980;25(Dec):346. 18. Layde PM, et al. J R Coll Gen Pract. 1983;33(Feb):75. 19. Rosenberg L, et al. JAMA. 1985;253(May 24/31):2965. 20. Mant D, et al. J Epidemiol Community Health. 1987;41 (Sept):215. 21. Croft P, et al. Br Med J. 1989;298 (Jan 21):165. 22. Goldbaum GM, et al. JAMA. 1987;258(Sept 11):1339. 23. Bradley DD, et al. N Engl J Med. 1978;299(July 6):17. 24. Tikkanen MJ. J Reprod Med. 1986;31(Sept suppl):898. 25. Lipson A, et al. Contraception. 1986;34(Aug):121. 26. Burkman RT, et al. Obstet Gynecol. 1988; 71(Jan):33. 27. Knopp RH, J Reprod Med. 1986;31(Sept Suppl):913. 28. Krauss RM, et al. Am J Obstet Gynecol. 1983;145(Feb 15):446. 29. Wahl P, et al. N Engl J Med. 1983;308(April 14):862. 30.Wynn V, et al. Am J Obstet Gynecol. 1982;142(March 15):766. 31. LaRosa JC. J Reprod Med. 1986;31(Sept suppl):906. 32. Wynn V, et al. J Reprod Med. 1986;31(Sept Suppl):892. 33. Royal College of General Practitioners. J R Coll Gen Pract. 1967;13(May):267. 34. Inman WHW, et al. Br Med J. 1968;2(April 27):193. 35. Vessey MP, et al. Br Med J. 1968;2(April 27):199. 36. Vessey MP, et al. Br Med J. 1969;2(June 14):651. 37. Sartwell PE, et al. Am J Epidemiol. 1969;90(Nov):365. 38. Vessey MP, et al. Br Med J. 1970;3(July 18):123. 39. Greene GR, et al. Am J Public Health. 1972;62(May):680. 40. Boston Collaborative Drug Surveillance Programme. Lancet. 1973;1(June 23):1399. 41. Stolley PD, et al. Am J Epidemiol. 1975;102(Sept):197. 42. Vessey MP, et al. J Biosoc Sci. 1976;8(Oct):373. 43. Kay CR, J R Coll Gen Pract. 1978;28(July):393. 44. Petitti DB, et al. Am J Epidemiol. 1978;108 (Dec):480. 45. Maquire MG, et al. Am J Epidemiol. 1979;110(Aug):188. 46. Petitti DB, et al. JAMA. 1979;242(Sept 14):1150. 47. Porter JB, et al. Obstet Gynecol. 1982;59(March):299. 48. Porter JB, et al. Obstet Gynecol. 1985;66(July):1. 49. Vessey MP, et al. Br Med J. 1986;292(Feb 22):526. 50. Hoover R, et al. Am J Public Health. 1978;68(April):335. 51. Vessey MP, Br J Fam Plann. 1980;6(Oct suppl):1. 52. Collaborative Group for the Study of Stroke in Young Women. N Engl J Med. 1973;288(April 26):871. 53. Royal College of General Practitioners. Oral Contraceptives and Health. New York, NY: Pitman Publ Corp; May 1974. 54. Collaborative Group for the Study of Stroke in Young Women. JAMA. 1975;231(Feb 17):718. 55. Beral V. Lancet. 1976;2(Nov 13):1047. 56. Vessey MP, et al. Lancet. 1977;2(Oct 8):731; and 1981;1(March 7):549. 57. Petitti DB, et al. Lancet. 1978;2(July 29):234. 58. Inman WHW. Br Med J. 1979;2(Dec 8):1468. 59. Vessey MP, et al. Br Med J. 1984; 289(Sept 1):530. 60. Inman WHW, et al. Br Med J. 1970;2(April 25):203. 61. Meade TW, et al. Br Med J. 1980;280(May 10):1157. 62. Bottiger LE, et al. Lancet. 1980;1(May 24):1097. 63. Kay CR. Am J Obstet Gynecol. 1982;142(March 15):762. 64. Vessey MP, et al. Br Med J. 1986;292(Feb 22):526. 65. Gordon T, et al. Am J Med. 1977;62(May):707. 66. Beral V, et al. Lancet. 1977;2(Oct 8):727. 67. Ory H. Fam Plann Perspect. 1983;15(March-April):57. 68. Arthes FG, et al. Cancer. 1971;28 (Dec):1391. 69. Vessey MP, et al. Br Med J. 1972;3(Sept 23):719. 70. Boston Collaborative Drug Surveillance Program. N Engl J Med. 1974;290(Jan 3):15.71. Vessey MP, et al. Lancet. 1975;1(April 26):941. 72. Casagrande J, et al. J Natl Cancer Inst. 1976;56(April):839. 73. Kelsey, JL, et al. Am J Epidemiol. 1978;107(March):236. 74. Kay CR, Br Med J. 1981;282(June 27):2089. 75. Vessey MP, et al. Br Med J. 1981;282(June 27):2093. 76. The Cancer and Steroid Hormone Study of the Centers for Disease Control and the National Institute of Child Health and Human Development. Oral contraceptive use and the risk of breast cancer. N Engl J Med. 1986;315(Aug 14):405. 77. Paul C, et al. Br Med J. 1986; 293 (Sept 20):723. 78. Miller DR, et al. Obstet Gynecol. 1986;68(Dec):863. 79. Pike MC, et al. Lancet. 1983;2(Oct 22):926. 80. McPherson K, et al. Br J Cancer. 1987;56(Nov):653. 81. Hoover R, et al. N Engl J Med. 1976;295(Aug 19):401. 82. Lees AW, et al. Int J Cancer. 1978;22(Dec):700. 83. Brinton LA, et al. J Natl Cancer Inst. 1979;62(Jan):37. 84. Black MM. Pathol Res Pract. 1980;166:491; and Cancer. 1980;46(Dec):2747; and Cancer. 1983;51(June):2147. 85. Thomas DB. JNCI. 1993;85 (March 3):359. 86. Brinton LA, et al. Int J Epidemiol. 1982;11(Dec):316. 87. Harris NV, et al. Am J Epidemiol. 1982;116(Oct):643. 88. Jick H, et al. Am J Epidemiol. 1980;112(Nov):577. 89. McPherson K, et al. Lancet. 1983;2(Dec 17):1414. 90. Hoover R, et al. J Natl Cancer Inst. 1981; 67(Oct):815. 91. Jick H, et al. Am J Epidemiol. 1980; 112(Nov):586. 92. Meirik O, et al. Lancet. 1986;2 (Sept 20):650. 93. Fasal E, et al. J Natl Cancer Inst. 1975;55(Oct):767. 94. Paffenbarger RS, et al. Cancer. 1977;39(April suppl):1887. 95. Stadel BV, et al. Contraception. 1988;38(Sept):287. 96. Miller DR, et al. Am J Epidemiol. 1989;129(Feb):269. 97. Kay CR, et al. Br J Cancer. 1988;58(Nov):675. 98. Miller DR, et al. Obstet Gynecol. 1986;68(Dec):863. 99. Hulka BS, et al. Cancer. 1994;74(August 1 suppl):1111. 100. Chilver CED, et al. Br J Cancer. 1994;67(May):922. 101. Huggins GR, et al. Fertil Steril. 1987;47(May):733. 102. Pike MC, et al. Br J Cancer. 1981;43(Jan):72. 103. Ory H, et al. Am J Obstet Gynecol. 1976;124(March 15):573. 104. Stern E, et al. Science. 1977;196(June 24):1460. 105. Pertiz E, et al. Am J Epidemiol. 1977;106(Dec):462. 106. Ory HW, et al. In: Garattini S, Berendes H, eds. Pharmacology of Steroid Contraceptive Drugs. New York, NY: Raven Press; 1977:211-224. 107. Meisels A, et al. Cancer. 1977;40(Dec):3076. 108. Goldacre MJ, et al. Br Med J. 1978;1(March 25):748. 109. Swan SH, et al. Am J Obstet Gynecol. 1981;139(Jan 1):52. 110. Vessey MP, et al. Lancet. 1983;2(Oct 22):930. 111. Dallenbach-Hellweg G. Pathol Res Pract. 1984;179:38. 112. Thomas DB, et al. Br Med J. 1985;290(March 30):961. 113. Brinton LA, et al. Int J Cancer. 1986;38(Sept):339. 114. Ebeling K, et al. Int J Cancer. 1987;39(April):427. 115. Beral V, et al. Lancet. 1988;2(Dec 10):1331. 116. Baum JK, et al. Lancet. 1973;2(Oct 27):926. 117. Edmondson HA, et al. N Engl J Med. 1976;294(Feb 26):470. 118. Bein NN, et al. Br J Surg. 1977;64(June):433. 119. Klatskin G. Gastroenterology. 1977;73(Aug):386. 120. Rooks JB, et al. JAMA. 1979;242(Aug 17):644. 121. Sturtevant FM. In: Moghissi K, ed. Controversies in Contraception, Baltimore, MD; Williams & Wilkins; 1979:93-150. 122. Henderson BE, et al. Br J Cancer. 1983;48(July):437. 123. Neuberger J, et al. Br Med J. 1986;292(May 24):1355. 124. Forman D, et al. Br Med J. 1986;292(May 24):1357. 125. La Vecchia C, et al. Br J Cancer. 1989;59(March):460. 126. Savolainen E, et al. Am J Obstet Gynecol 1981;140(July 1):521. 127. Ferencz C, et al. Teratology. 1980;21(April):225. 128. Rothman KJ, et al. Am J Epidemiol. 1979;109(April):433. 129. Harlap S, et al. Obstet Gynecol. 1980;55(April):447.130. Layde PM, et al. J Epidemiol Community Health. 1982;36(Dec):274. 131. Rome Group for the Epidemiology and Prevention of Cholelithiasis (GREPCO). Am J Epidemiol. 1984;119(May):796. 132. Strom BL, et al. Clin Pharmacol Ther. 1986;39(March):335. 133. Wynn V. In: Bardin CE, et al, eds. Progesterone and Progestins. New York, NY: Raven Press; 1983:395-410. 134. Perlman JA, et al. J Chron Dis. 1985;38(Oct):857. 135. Powell MG, et al. Obstet Gynecol. 1984;63(June):764. 136. Wynn V, et al. Lancet. 1966;2(Oct 1):720. 137. Fisch IR, et al. JAMA. 1977;237(June 6):2499. 138. Kay CR. Lancet. 1977;1(March 19):624. 139. Laragh JH. Am J Obstet Gynecol. 1976;126(Sept 1):141. 140. Ramcharan S. In: Garattini S, Berendes HW, eds. Pharmacology of Steroid Contraceptive Drugs. New York, NY: Raven Press; 1977:277-288. 141. Laumas KR, et al. Am J Obstet Gynecol. 1967;98(June 1):411. 142. Saxena BN, et al. Contraception. 1977;16(Dec):605. 143. Nilsson S, et al. Contraception. 1978;17(Feb):131. 144. Washington AE, et al. JAMA. 1985;253(April 19):2246. 145. Louv WC, et al. Am J Obstet Gynecol. 1989;160(Feb):396. 146. Francis WG, et al. Can Med Assoc J. 1965;92(Jan 23):191. 147. Verhulst HL, et al. J Clin Pharmacol. 1967:7(Jan-Feb):9. 148. Ory HW, Fam Plann Perspect. 1982;14(July-Aug):182. 149. Ory HW, et al. Making Choices: Evaluating the Health Risks and Benefits of Birth Control Methods. New York, NY: The Alan Guttmacher Institute; 1983. 150. Palmer JR, et al. Am J Epidemiol. 1989;130(Nov):878. 151. Romieu I, et al. J Natl Cancer Inst. 1989;81(Sept):1313. 152. Porter JB, et al. Obstet Gynecol. 1987;70(July):29. 153. Olsson H, et al. Cancer Detect Prev. 1991;15:265. 154. Delgado-Rodriguez M, et al. Rev Epid m Sant Publ. 1991;39:165. 155. Clavel F, et al. Int J Epidemiol. 1991;20(March):32. 156. Brinton LA, et al. JNCI. 1995;87(June 7):827. 157. Thomas DB, et al. Br J Cancer. 1992;65(January):108. 158. Thomas DB, et al. Cancer Causes Cont. 1991;2(Nov):389. 159. Weinstein AL, et al. Epidemiology. 1991;2(Sept):353. 160. Ranstam J, et al. Anticancer Res. 1991;11(Nov- Dec):2043. 161. Ursin G. et al. Epidemiology. 1992;3(Sept):414. 162. White E, et al. JNCI. 1994;86(April 6):505. 163. Mann R, et al. Oral contraceptives and Breast Cancer. Park Ridge, NJ: The Parthenon Publishing Group Inc.; 1990. 164. Institute of Medicine. Committee on the Relationship Between Oral Contraceptives and Breast Cancer. Oral Contraceptives and Breast Cancer. Washington, DC: National Academy Press; 1991. 165. Harlap S. J Reprod Med. 1991;36(May):374. 166. Rushton L, et al. Br J Obstet Gynaecol. 1992;99(March):239. 167. Colditz G. Cancer. 1993;71(Feb 15 suppl):1480.

BRIEF SUMMARY OF PATIENT WARNINGS

This product (like all oral contraceptives) is intended to prevent pregnancy. It does not protect against HIV infection (AIDS) and other sexually transmitted diseases.

In the detailed leaflet, "What You Should Know About Oral Contraceptives," which you have received, the risks and benefits of oral contraceptives are discussed in much more detail. That leaflet also provides information on other forms of contraception. Please take time to read it carefully for it may have been recently revised.

If you have any questions or problems regarding this information, contact your doctor.

Oral contraceptives, also known as "birth control pills" or "the pill," are taken to prevent pregnancy and, when taken correctly, have a failure rate of about 1% per year when used without missing any pills. The typical failure rate of large numbers of pill users is less than 3% per year when women who miss pills are included. However, forgetting to take pills considerably increases the chances of pregnancy.

For most women, oral contraceptives are free of serious or unpleasant side effects. However, oral contraceptive use is associated with certain serious diseases or conditions that can cause severe disability or death, though rarely. There are some women who are at high risk of developing certain serious diseases that can be life-threatening or may cause temporary or permanent disability. The risks associated with taking oral contraceptives increase significantly if you:

● smoke, or

● have high blood pressure, diabetes, high cholesterol, or are overweight, or

● have or have had clotting disorders, heart attack, stroke, angina pectoris (chest pains on exertion), cancer of the breast or sex organs, jaundice (yellowing of the skin or whites of the eyes), or malignant (cancerous) or benign (noncancerous) liver tumors.

Women should not use oral contraceptives if they suspect they are pregnant or if they have unexplained vaginal bleeding.

Most side effects of the pill are not serious. The most common effects are nausea, vomiting, bleeding between menstrual periods, weight gain, breast tenderness, and difficulty wearing contact lenses. These side effects, especially nausea and vomiting, may subside within the first three months of use.

Proper use of oral contraceptives requires that they be taken under your doctor's continuing supervision, because they can be associated with serious side effects. The serious side effects of the pill occur very infrequently, especially if you are in good health and are young. However, you should know that the following medical conditions have been associated with or made worse by the pill, and that certain of the risks may persist after use of the pill has been discontinued:

1. Blood clots in the legs, arms, lungs, heart (heart attack), eyes, abdomen, or elsewhere in the body. As mentioned above, smoking increases the risk of heart attacks and strokes and subsequent serious medical consequences.

2. Stroke, due to a blood clot, or to bleeding in the brain (hemorrhage) as a result of bursting of a blood vessel. Stroke can lead to paralysis in all or part of the body, or to death.

3. Liver tumors, which may rupture and cause severe bleeding and death. A possible, but not definite, association has also been found with the pill and liver cancer. However, with or without use of the pill, liver cancers are extremely rare in the United States.

4. High blood pressure, although blood pressure ordinarily, but not always, returns to original levels when the pill is stopped.

5. Gallbladder disease, which might require surgery.

The symptoms associated with these serious side effects are discussed in the detailed leaflet given to you with your supply of pills. Notify your doctor or health care provider if you notice any unusual physical disturbances while taking the pill. In addition, you should be aware that drugs such as antiepileptics, antibiotics (especially rifampin), as well as certain other drugs, may decrease oral contraceptive effectiveness.

There is a conflict among studies regarding breast cancer and oral contraceptive use. Some studies have reported an increase in the risk of developing breast cancer, particularly at a younger age. This increased risk appears to be related to duration of use. The majority of studies have found no overall increase in the risk of developing breast cancer. Some studies have found an increase in the incidence of cancer of the cervix in women who use oral contraceptives. However, this finding may be related to factors other than the use of oral contraceptives. There is insufficient evidence to rule out the possibility that pills may cause such cancers.

Taking the pill may provide some important non-contraceptive benefits. These include less painful menstruation, less menstrual blood loss and anemia, less risk of fibroids, pelvic infections, and noncancerous breast disease, and less risk of cancer of the ovary and of the lining of the uterus (womb).

Be sure to discuss any medical condition you may have with your health care provider. He or she will take a medical and family history before prescribing oral contraceptives and will also examine you. The physical examination may be delayed to another time if you request it and the health care provider believes that it is a good medical practice to postpone it. You should be re-examined at least once a year while taking oral contraceptives. The detailed patient information leaflet gives you further information that you should read and discuss with your health care provider.

DETAILED PATIENT LABELING:

WHAT YOU SHOULD KNOW ABOUT ORAL CONTRACEPTIVES

This product (like all oral contraceptives) is intended to prevent pregnancy. It does not protect against HIV infection (AIDS) and other sexually transmitted diseases.

INTRODUCTION

It is important that any woman who considers using an oral contraceptive understand the risks involved. Although the oral contraceptives have important advantages over other methods of contraception, they have certain risks that no other method has. Only you and your physician can decide whether the advantages are worth these risks. This leaflet will tell you about the most important risks. It will explain how you can help your doctor prescribe the pill as safely as possible by telling him/her about yourself and being alert for the earliest signs of trouble. And it will tell you how to use the pill properly so that it will be as effective as possible. THERE IS MORE DETAILED INFORMATION AVAILABLE IN THE LEAFLET PREPARED FOR DOCTORS. Your pharmacist can show you a copy; you may need your doctor's help in understanding parts of it.

This leaflet is not a replacement for a careful discussion between you and your health care provider. You should discuss the information provided in this leaflet with him or her, both when you first start taking the pill and during your revisits. You should also follow your health care provider's advice with regard to regular check-ups while you are on the pill.

If you do not have any of the conditions listed below and are thinking about using oral contraceptives, to help you decide, you need information about the advantages and risks of oral contraceptives and of other contraceptive methods as well. This leaflet describes the advantages and risks of oral contraceptives. Except for sterilization, the intrauterine device (IUD), and abortion, which have their own specific risks, the only risks of other methods are those due to pregnancy should the method fail. Your doctor can answer questions you may have with respect to other methods of contraception, and further questions you may have on oral contraceptives after reading this leaflet.

WHAT ARE ORAL CONTRACEPTIVES?

The most common type of oral contraceptive, often simply called "the pill," is a combination of estrogen and progestogen, the two kinds of female hormones. The amount of estrogen and progestogen can vary, but the amount of estrogen is more important because both the effectiveness and some of the dangers of the pill have been related to the amount of estrogen. The pill works principally by preventing release of an egg from the ovary during the cycle in which the pills are taken.

EFFECTIVENESS OF ORAL CONTRACEPTIVES

The pill is one of the most effective methods of birth control. When they are taken correctly, without missing any pills, the chance of becoming pregnant is less than 1% (1 pregnancy per 100 women per year of use) when used perfectly, without missing any pills. Typical failure rates are actually about 3% per year. The chance of becoming pregnant increases with each missed pill during a menstrual cycle.

In comparison, typical failure rates for other methods of birth control during the first year of use are as follows:

(A) Among typical couples who initiate use of a method (not necessarily for the first time), the percentage who experience an accidental pregnancy during the first year if they do not stop use for any other reason.

(B) Among couples who initiate use of a method (not necessarily for the first time) and who use it perfectly (both consistently and correctly), the percentage who experience an accidental pregnancy during the first year if they do not stop use for any other reason.

(C) Among couples attempting to avoid pregnancy, the percentage who continue to use a method for one year.

(D) The percents becoming pregnant in columns (2) and (3) are based on data from populations where contraception is not used and from women who cease using contraception in order to become pregnant. Among such populations, about 89% become pregnant within one year. This estimate was lowered slightly (to 85%) to represent the percent who would become pregnant within one year among women now relying on reversible methods of contraception if they abandoned contraception altogether.

(E) Foams, creams, gels, vaginal suppositories, and vaginal film.

(F) Cervical mucus (ovulation) method supplemented by calendar in the pre-ovulatory and basal body temperature in the post-ovulatory phases.

(G) With spermicidal cream or jelly.

(H) Without spermicides.

(I) The treatment schedule is one dose within 72 hours after unprotected intercourse and a second dose 12 hours after the first dose. The Food and Drug Administration has declared the following brands of oral contraceptives to be safe and effective for emergency contraception: Ovral (1 dose is 2 white pills), Alesse (1 dose is 5 pink pills), Nordette or Levlen (1 dose is 2 light-orange pills), Lo/Ovral (1 dose is 4 white pills), Triphasil or Tri-Levlen (1 dose is 4 yellow pills).

(J) However, to maintain effective protection against pregnancy, another method of contraception must be used as soon as menstruation resumes, the frequency or duration of breastfeeds is reduced, bottle feeds are introduced, or the baby reaches six months of age.

WHO SHOULD NOT TAKE ORAL CONTRACEPTIVES

Some women should not use the pill. For example, you should not take the pill if you are pregnant or think you may be pregnant. You should also not use the pill if you have any of the following conditions:

● Heart attack or stroke (blood clot or hemorrhage in the brain), currently or in the past.

● Blood clots in the legs (thrombophlebitis), lungs (pulmonary embolism), eyes, or elsewhere in the body, currently or in the past.

● Chest pain (angina pectoris), currently or in the past.

● Known or suspected breast cancer or cancer of the lining of the uterus (womb), cervix, or vagina, currently or in the past.

● Unexplained vaginal bleeding (until a diagnosis is reached by your doctor).

● Yellowing of the whites of the eyes or of the skin (jaundice) during pregnancy or during previous use of the pill.

● Liver tumor (whether cancerous or not), currently or in the past.

● Take any Hepatitis C drug combination containing obitasvir/paritaprevir/ritonavir with or without dasabuvir. This may increase levels of the liver enzyme "alanine aminotransferase" (ALT) in the blood.

● Known or suspected pregnancy (one or more menstrual periods missed).

Tell your health care provider if you have ever had any of these conditions. He or she can recommend a safer method of birth control.

OTHER CONSIDERATIONS BEFORE TAKING ORAL CONTRACEPTIVES

Tell your health care provider if you have or have had any of the following conditions, as he or she will want to watch them closely or they might cause him or her to suggest using another method of contraception:

● Breast nodules (lumps), fibrocystic disease (breast cysts), abnormal mammograms (x-ray pictures of the breast), or abnormal Pap smears

● Diabetes

● High blood pressure

●High blood cholesterol or triglycerides

● Migraine or other headaches or epilepsy

● Mental depression

● Gallbladder, heart, or kidney disease

● History of scanty or irregular menstrual periods

● Problems during a prior pregnancy

● latest post-marketing stability data summary Fibroid tumors of the womb

● History of jaundice (yellowing of the whites of the eyes or of the skin)

● Varicose veins

● Tuberculosis

● Plans for elective surgery

Women with any of these conditions should be checked often by their health care provider if they choose to use oral contraceptives.

Also, be sure to tell your doctor if you smoke or are on any medications.

RISKS OF TAKING ORAL CONTRACEPTIVES

1. Risk of developing blood clots. Blood clots and blockage of blood vessels are the most serious side effects of taking oral contraceptives. In particular, a clot in the legs can cause thrombophlebitis and a clot that travels to the lungs can cause a sudden blocking of the vessel carrying blood to the lungs. Rarely, clots occur in the blood vessels of the eye and may cause blindness, double vision, or impaired vision.

If you take oral contraceptives and need elective surgery, need to stay in bed for a prolonged illness, or have recently delivered a baby, you may be at risk of developing blood clots. You should consult your doctor about stopping oral contraceptives 3 to 4 weeks before surgery and not taking oral contraceptives for 2 weeks after surgery or during bed rest. You should also not take oral contraceptives soon after delivery of a baby. It is advisable to wait for at least 4 weeks after delivery if you are not breast feeding. If you are breast feeding, you should wait until you have weaned your child before using the pill. (See also the section on Breast feeding in GENERAL PRECAUT IONS.)

The risk of circulatory disease in oral contraceptive users may be higher in users of high-dose pills and may be greater with longer duration of oral contraceptive use. In addition, some of these increased risks may continue for a number of years after stopping oral contraceptives. The risk of abnormal blood clotting increases with age in both users and nonusers of oral contraceptives, but the increased risk from the oral contraceptive appears to be present at all ages. For women aged 20 to 44 it is estimated that about 1 in 2,000 using oral contraceptives will be hospitalized each year because of abnormal clotting. Among nonusers in the same age group, about 1 in 20,000 would be hospitalized each year. For oral contraceptive users in general, it has been estimated that in women between the ages of 15 and 34, the risk of death due to a circulatory disorder is about 1 in 12,000 per years, whereas for nonusers the rate is about 1 in 50,000 per year. In the age group 35 to 44, the risk is estimated to be about 1 in 2,500 per year for oral contraceptive users and about 1 in 10,000 per year for nonusers.

2. Heart attacks and strokes. Oral contraceptives may increase the tendency to develop strokes (stoppage by blood clots or rupture of blood vessels of the brain) and angina pectoris and heart attacks (blockage of blood vessels of the heart). Any of these conditions can cause death or permanent disability.

Smoking greatly increases the possibility of suffering heart attacks and strokes. Furthermore, smoking and the use of oral contraceptives greatly increases the chances of developing and dying of heart disease.

3. Gallbladder disease. Oral contraceptive users probably have a greater risk than non-users of having gallbladder disease, although this risk may be related to pills containing high doses of estrogens.

4. Liver tumors. In rare cases, oral contraceptives can cause benign but dangerous liver tumors. These benign tumors can rupture and cause fatal internal bleeding. In addition, a possible but not definite association has been found with the pill and liver cancers in several studies, in which a few women who developed these very rare cancers were found to have used oral contraceptives for long periods. However, liver cancers are rare.

5. Cancer of the reproductive organs and breasts. There is conflict among studies regarding breast cancer and oral contraceptive use. Some studies have reported an increase in the risk of developing breast cancer, particularly at a younger age. This increased risk appears to be related to duration of use. The majority of studies have found no overall increase in the risk of developing breast cancer. Women who use oral contraceptives and have a strong family history of breast cancer or who have had breast nodules or abnormal mammograms should be closely followed by their doctors.

Some studies have found an increase in the incidence of cancer of the cervix in women who use oral contraceptives. However, this finding may be related to factors other than the use of oral contraceptives. There is insufficient evidence to rule out the possibility that pills may cause such cancers.

ESTIMATED RISK OF DEATH FROM BIRTH CONTROL METHOD OR PREGNANCY

All methods of birth control and pregnancy are associated with a risk of developing certain diseases that may lead to disability or death. An estimate of the number of deaths associated with different methods of birth control and pregnancy has been calculated and is shown in the following table.

In the above table, the risk of death from any birth control method is less than the risk of childbirth, except for oral contraceptive users over the age of 35 who smoke and pill users over the age of 40 even if they do not smoke. It can be seen in the table that for women aged 15 to 39, the risk of death was highest with pregnancy (7-26 deaths per 100,000 women, depending on age). Among pill users who do not smoke, the risk of death was always lower than that associated with pregnancy for any age group, although over the age of 40, the risk increases to 32 deaths per 100,000 women, compared to 28 associated with pregnancy at that age. However, for pill users who smoke and are over the age of 35, the estimated number of deaths exceeds those for other methods of birth control. If a woman is over the age of 40 and smokes, her estimated risk of death is four times higher (117/100,000 women) than the estimated risk associated with pregnancy (28/100,000) in that age group.

The suggestion that women over 40 who don't smoke should not take oral contraceptives is based on information from older high-dose pills and on less selective use of pills than is practiced today. An Advisory Committee of the FDA discussed this issue in 1989 and recommended that the benefits of oral contraceptive use by healthy, nonsmoking women over 40 years of age may outweigh the possible risks. However, all women, especially older women, are cautioned to use the lowest dose pill that is effective.

WARNING SIGNALS

If any of these adverse effects occur while you are taking oral contraceptives, call your doctor immediately:

● Sharp chest pain, coughing up blood, or sudden shortness of breath (indicating a possible blood clot in the lung).

● Pain in the calf (indicating a possible blood clot in the leg).

● Crushing chest pain or heaviness in the chest (indicating a possible heart attack).

● Sudden severe headache or vomiting, dizziness or fainting, disturbances of vision or speech, or numbness in an arm or leg (indicating a possible stroke).

● Sudden partial or complete loss of vision (indicating a possible blood clot in the blood vessels of the eye).

● Breast lumps (indicating possible breast cancer or fibrocystic disease of the breast). Ask your doctor or health care provider to show you how to examine your own breasts.

● Severe pain or tenderness or a mass in the stomach area (indicating a possible ruptured liver tumor).

● Difficulty in sleeping, weakness, lack of energy, fatigue, or change in mood (possibly indicating severe depression).

● Jaundice or a yellowing of the skin or eyeballs, accompanied frequently by fever, fatigue, loss of appetite, dark-colored urine, or light-colored bowel movements (indicating possible liver problems).

● Unusual swelling.

● Other unusual conditions.

SIDE EFFECTS OF ORAL CONTRACEPTIVES

1. Vaginal bleeding.

Spotting. This is a slight staining between your menstrual periods that may not even require a pad. Some women spot even though they take their pills exactly as directed. Many women spot although they have never taken the pills. Spotting does not mean that your ovaries are releasing an egg. Spotting may be the result of irregular pill-taking. Getting back on schedule will usually stop it.

If you should spot while taking the pills, you should not be alarmed, because spotting usually stops by itself within a few days. It seldom occurs after the first pill cycle. Consult your doctor if spotting persists for more than a few days or if it occurs after the second cycle.

Unexpected (breakthrough) bleeding. Unexpected (breakthrough) bleeding does not mean that your ovaries have released an egg. It seldom occurs, but when it does happen it is most common in the first pill cycle. It is a flow much like a regular period, requiring the use of a pad or tampon.

If you experience breakthrough bleeding use a pad or tampon and continue with your schedule. Usually your periods will become regular within a few cycles. Breakthrough bleeding will seldom bother you again.

Consult your doctor or health care provider if breakthrough bleeding is heavy, does not stop within a week, or if it occurs after the second cycle.

2. Contact lenses. If you wear contact lenses and notice a change in vision or an inability to wear your lenses, contact your doctor or health care provider.

3. Fluid retention or raised blood pressure. Oral contraceptives may cause edema (fluid retention), with swelling of the fingers or ankles. If you experience fluid retention, contact your doctor or health care provider. Some women develop high blood pressure while on the pill, which ordinarily, but not always, returns to the original levels when the pill is stopped. High blood pressure predisposes one to strokes, heart attacks, kidney disease, and other diseases of the blood vessels.

4. Melasma. A spotty darkening of the skin is possible, particularly of the face. This may persist after the pill is discontinued.

5. Other side effects. Other side effects may include nausea and vomiting, change in appetite, headache, nervousness, depression, dizziness, loss of scalp hair, rash, and vaginal infections.

If any of these, or other, side effects occur, call your doctor or health care provider.

GENERAL PRECAUTIONS

1. Missed periods and use of oral contraceptives before or during early pregnancy.

Occasionally women who are taking the pill miss periods. It has been reported to occur as frequently as several times each year in some women, depending on various factors such as age and prior history (your doctor is the best source of information about this). The pill should not be used when you are pregnant or suspect you may be pregnant. Very rarely, women who are using the pill as directed become pregnant. The likelihood of becoming pregnant is higher if you occasionally miss one or two pills. Therefore, if you miss a period you should consult your physician before continuing to take the pill. If you miss a period, especially if you have not taken the pill regularly, you should use an alternative method of contraception until pregnancy has been ruled out; if you have missed more than one pill at any time, you should immediately start using an additional method of contraception and complete your pill cycle.

There is no conclusive evidence that oral contraceptive use is associated with an increase in birth defects when taken inadvertently during early pregnancy. Previously, a few studies had reported that oral contraceptives might be associated with birth defects, but these findings have not been seen in more recent studies. Nevertheless, oral contraceptives or any other drugs should not be used during pregnancy unless clearly necessary and prescribed by your doctor. You should check with your doctor about risks to your unborn child of any medication taken during pregnancy.

2. Breast feeding.

If you are breast feeding, consult your doctor before starting oral contraceptives. Some of the drug will be passed on to the child in the milk. A few adverse effects on the child have been reported, including yellowing of the skin (jaundice) and breast enlargement. In addition, oral contraceptives may decrease the amount and quality of your milk. If possible, do not use oral contraceptives while breast feeding. You should use another method of contraception since breast feeding provides only partial protection from becoming pregnant and this partial protection decreases significantly as you breast feed for longer periods of time. You should consider starting oral contraceptives only after you have weaned your child completely.

3. Laboratory tests.

If you are scheduled for any laboratory tests, tell your doctor you are taking birth control pills. Certain blood tests may be affected by birth control pills.

4. Drug interactions.

Certain drugs may interact with birth control pills to make them less effective in preventing pregnancy or cause an increase in breakthrough bleeding. Such drugs include rifampin, drugs used for epilepsy such as barbiturates (for example, phenobarbital) and phenytoin (Dilantin is one brand of this drug), phenylbutazone (Butazolidin is one brand), Rezulin (troglitazone) a hypoglycemic, and possibly certain antibiotics. You may need to use additional contraception when you take drugs that can make oral contraceptives less effective.

Oral contraceptives may have an influence upon the way other drugs act. Check with your doctor if you are taking any other drugs while you are on the pill.

HOW TO TAKE THE PILL

IMPORTANT POINTS TO REMEMBER

BEFORE YOU START TAKING YOUR PILLS:

1. BE SURE TO READ THESE DIRECTIONS:

● Before you start taking your pills.

● Anytime you are not sure what to do.

2. THE RIGHT WAY TO TAKE THE PILL IS TO TAKE ONE PILL EVERY DAY AT THE SAME TIME.

If you miss pills you could get pregnant. This includes starting the pack late. The more pills you miss, the more likely you are to get pregnant.

3. MANY WOMEN HAVE SPOTTING OR LIGHT BLEEDING, OR MAY FEEL SICK TO THEIR STOMACH DURING THE FIRST 1-3 PACKS OF PILLS.

If you feel sick to your stomach, do not stop taking the pill. The problem will usually go away. If it doesn't go away, check with your doctor or clinic.

4. MISSING PILLS CAN ALSO CAUSE SPOTTING OR LIGHT BLEEDING, even when you make up these missed pills.

On the days you take 2 pills to make up for missed pills, you could also feel a little sick to your stomach.

5. IF YOU HAVE VOMITING OR DIARRHEA, for any reason, or IF YOU TAKE SOME MEDICINES, including some antibiotics, your pills may not work as well.

Use a backup method (such as condoms, foam, or sponge) until you check with your doctor or clinic.

6. IF YOU HAVE TROUBLE REMEMBERING TO TAKE THE PILL, talk to your doctor or clinic about how to make pill-taking easier or about using another method of birth control.

7. IF YOU HAVE ANY QUESTIONS OR ARE UNSURE ABOUT THE INFORMATION IN THIS LEAFLET, call your doctor or clinic.

BEFORE YOU START TAKING YOUR PILLS

1. DECIDE WHAT TIME OF DAY YOU WANT TO TAKE YOUR PILL.

It is important to take it at about the same time every day.

2. LOOK AT YOUR PILL PACK:

Your tablet dispenser consists of a plastic compact and a blister pack containing 28 pills. The 28 tablets are arranged in four numbered rows with the days of the week embossed on the plastic compact just above the tablets, starting with Sunday on the left.

The Zovia 1/35 tablet dispenser contain 21 pale pink active tablets arranged in three numbered rows of 7 tablets each, followed by a fourth row of 7 white placebo (inactive) tablets (see graphic below).

The 28-pill pack has 21 pale pink "active" pills (with hormones) to take for 3 weeks, followed by 1 week of reminder white placebo pills (without hormones). To remove a pill press down on it with the flat of your finger. The pill will drop through a hole in the bottom of the dispenser.

3. ALSO FIND:

● Where on the pack to start taking pills.

● In what order to take the pills (left to right).

Begin the 28-pill pack with the first pill in Row 1 and continue across Row 1 (Start 1). Repeat for Row 2, Row 3, and finally Row 4. Take all "active" pills (pale pink) before starting Row 4.

4. BE SURE YOU HAVE READY AT ALL TIMES:

● ANOTHER KIND OF BIRTH CONTROL (such as condoms, foam, or sponge) to use as a backup in case you miss pills.

● AN EXTRA, FULL PILL PACK.

WHEN TO START THE FIRST PACK OF PILLS

You have a choice of which day to start taking your first pack of pills. Zovia 1/35 is available in a compact blister card preset for a Sunday Start with the days of the week embossed on the plastic compact just above the tablets, starting with Sunday on the left.

Day 1 Start stickers are also provided. Decide with your doctor or clinic which is the best day for you. Pick a time of day which will be easy to remember.

DAY 1 START:

1. Pick the day label sticker that starts with the first day of your period (this is the day you start bleeding or spotting, even if it is almost midnight when the bleeding begins).

2. Place this day label sticker in the tablet dispenser over the area that has the days of the week (starting with Sunday) imprinted on the plastic compact.

Note: If the first day of your period is a Sunday, you can skip steps #1 and #2.

3. Take the first "active" pill (pale pink) of the first pack during the first 24 hours of your period.

4. You will not need to use a backup method of birth control, since you are starting the pill at the beginning of your period.

SUNDAY START:

1. Take the first "active" pill (pale pink) of the first pack on the Sunday after your period starts, even if you are still bleeding. If your period begins on Sunday, start the pack that same day.

2. Use another method of birth control as a backup method if you have sex anytime from the Sunday you start your first pack until the next Sunday (7 days). Condoms, foam, or the sponge are good backup methods of birth control.

WHAT TO DO DURING THE MONTH

1. TAKE ONE PILL AT THE SAME TIME EVERY DAY UNTIL THE PACK IS EMPTY.

● Do not skip pills even if you are spotting or bleeding between monthly periods or feel sick to your stomach (nausea).

● Do not skip pills even if you do not have sex very often.

2. WHEN YOU FINISH A PACK OR SWITCH YOUR BRAND OF 28-DAY PILLS: Start the next

pack on the day after your last "reminder" pill. Do not wait any days between 28-day packs.

WHAT TO DO IF YOU MISS PILLS

If you MISS 1"active" pill (pale pink):

1. Take it as soon as you remember. Take the next pill at your regular time. This means you may take 2 pills in 1 day.

2. You do not need to use a backup birth control method if you have sex.

If you MISS 2"active" pills (pale pink) in a row in WEEK 1 OR WEEK 2 of your pack:

1. Take 2 pills on the day you remember and 2 pills the next day.

2. Then take 1 pill a day until you finish the pack.

3. You MAY BECOME PREGNANT if you have sex in the 7 days after you miss pills. You MUST use another birth control method (such as condoms, foam, or sponge) as a backup for those 7 days.

If you MISS 2"active" pills (pale pink) in a row in THE 3rd WEEK:

1. If you are a Day 1 Starter:

THROW OUT the rest of the pill pack and start a new pack that same day.

If you are a Sunday Starter:

Keep taking 1 pill every day until Sunday.

On Sunday, THROW OUT the rest of the pack and start a new pack of pills that same day.

2. You may not have your period this month but this is expected. However, if you miss your period 2 months in a row, call your doctor or clinic because you might be pregnant.

3. You MAY BECOME PREGNANT if you have sex in the 7 days after you miss pills. You MUST use another birth control method (such as condoms, foam, or sponge) as a backup for those 7 days.

If you MISS 3 OR MORE "active" pills (pale pink) in a row (during the first 3 weeks):

1. If you are a Day 1 Starter:

THROW OUT the rest of the pill pack and start a new pack of pills that same day.

If you are a Sunday Starter:

Keep taking 1 pill every day until Sunday.

On Sunday, THROW OUT the rest of the pack and start a new pack of pills that same day.

2. You may not have your period this month but this is expected. However, if you miss your period 2 months in a row, call your doctor or clinic because you might be pregnant.

3. You MAY BECOME PREGNANT if you have sex in the 7 days after you miss pills. You MUST use another birth control method (such as condoms, foam, or sponge) as a backup for those 7 days.

A REMINDER:

If you forget any of the 7 white "reminder" pills in Week 4:

● THROW AWAY the pills you missed.

● Keep taking 1 pill each day until the pack is empty.

● You do not need a backup method.

FINALLY, IF YOU ARE STILL NOT SURE WHAT TO DO ABOUT THE PILLS YOU HAVE MISSED

● Use a BACKUP METHOD of birth control anytime you have sex.

● KEEP TAKING ONE "ACTIVE" PILL EACH DAY until you can reach your doctor or clinic.

PREGNANCY DUE TO PILL FAILURE

The incidence of pill failure resulting in pregnancy is approximately 1% (i.e., one pregnancy per 100 women per year) if taken every day as directed, but, because some women fail to follow the daily schedule, more typical failure rates are about 3%. If you become pregnant you should discuss your pregnancy with your doctor.

PREGNANCY AFTER STOPPING THE PILL

There may be some delay in becoming pregnant after you stop using oral contraceptives, especially if you had irregular menstrual cycles before you used oral contraceptives. It may be advisable to postpone conception until you begin menstruating regularly once you have stopped taking the pill and desire pregnancy.

There does not appear to be any increase in birth defects in newborn babies when pregnancy occurs after stopping the pill.

OVERDOSAGE

Serious ill effects have not been reported following ingestion of large doses of oral contraceptives by young children. Overdosage may cause nausea and withdrawal bleeding in females. In case of overdosage, contact your health care provider, pharmacist or Poison Control Center.

OTHER INFORMATION

Your health care provider will take a medical and family history before prescribing oral contraceptives and will also examine you. The physical examination may be delayed to another time if you request it and the health care provider believes that it is a good medical practice to postpone it. You should be re-examined at least once a year. Certain health problems or conditions in your medical or family history may require that your health care provider see you more frequently while you are taking the pill. Be sure to keep all appointments with your health care provider because this is a time to determine if there are early signs of side effects of oral contraceptive use.

Do not use the drug for any condition other than the one for which it was prescribed. This drug has been prescribed specifically for you; do not give it to others who may want birth control pills.

This product (like all oral contraceptives) is intended to prevent pregnancy. It does not protect against transmission of HIV (AIDS) and other sexually transmitted diseases such as chlamydia, genital herpes, genital warts, gonorrhea, hepatitis B, and syphilis.

HEALTH BENEFITS FROM ORAL CONTRACEPTIVES

In addition to preventing pregnancy, use of oral contraceptives may provide certain benefits. They are:

● Menstrual cycles may become more regular

● Blood flow during menstruation may be lighter and less iron may be lost. Therefore, anemia due to iron deficiency is less likely to occur

● Pain or other symptoms during menstruation may be encountered less frequently

● Ectopic (tubal) pregnancy may occur less frequently

● Noncancerous cysts or lumps in the breast may occur less frequently

● Acute pelvic inflammatory disease may occur less frequently

● Fibroids of the uterus (womb) may occur less frequently

● Oral contraceptive use may provide some protection against developing two forms of cancer: cancer of the ovaries and cancer of the lining of the uterus (womb)

If you want more information about birth control pills, ask your doctor or pharmacist. They have a more technical leaflet called the Professional Labeling, which you may wish to read. The Professional Labeling is also published in a book entitled Physicians' Desk Reference, available in many book stores and public libraries.

Keep this and all drugs out of the reach of children.

Be certain to read new revisions of this leaflet.

To report SUSPECTED ADVERSE REACTIONS, contact Mayne Pharma Toll-Free at 1-844-825-8500 or FDA at 1-800-FDA-1088 or www.fda.gov/medwatch.

Distributed by: Mayne Pharma

Greenville, NC 27834

I 0134 Iss. 07/2020 Rev.A